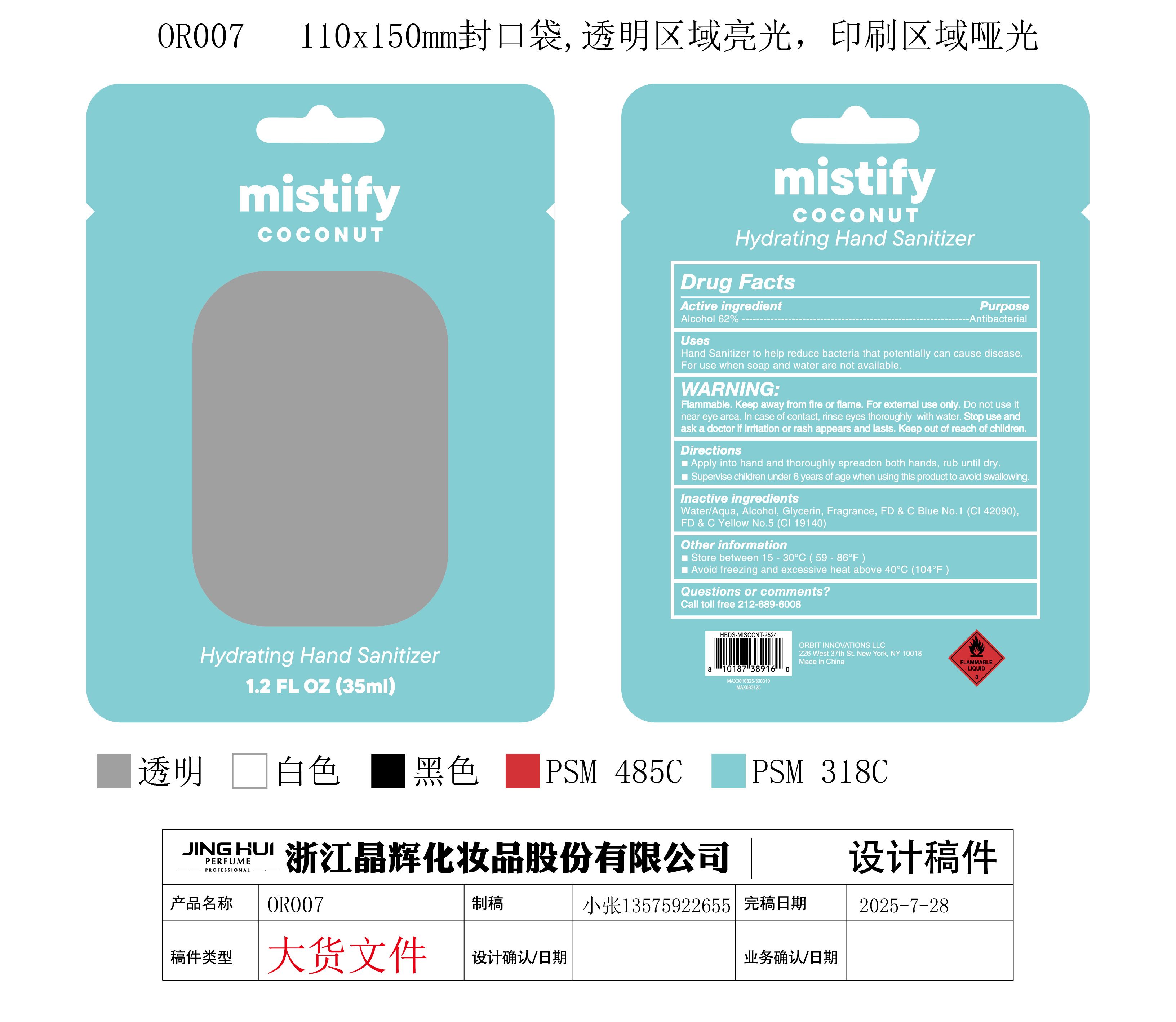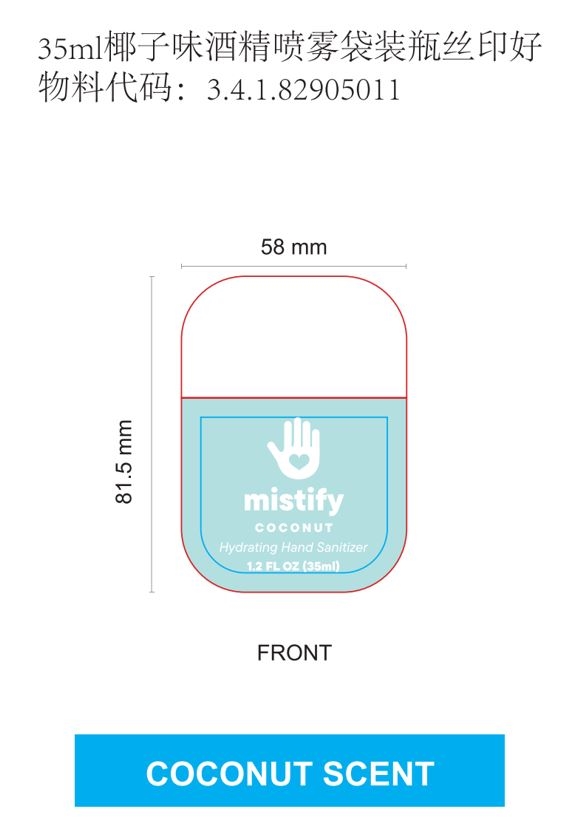 DRUG LABEL: Hand Sanitizer(COCONUT)
NDC: 73905-042 | Form: LIQUID
Manufacturer: ZHEJIANG JINGHUI COSMETICS SHARE CO.,LTD
Category: otc | Type: HUMAN OTC DRUG LABEL
Date: 20250924

ACTIVE INGREDIENTS: ALCOHOL 62 mL/100 mL
INACTIVE INGREDIENTS: GLYCERIN; AQUA; FD&C BLUE NO. 1; FD&C YELLOW NO. 5; COCONUT

73905-042-01 Hand Sanitizer(COCONUT)

This is a high - quality hand sanitizer crafted to meet the highest standards of hygiene and safety.
The hand sanitizer is produced using only the following United States Pharmacopoeia (USP) grade ingredients in the product formulation (percentage in the final product), in line with global best - practice guidelines:
Alcohol (ethanol) (USP or Food Chemical Codex (FCC) grade) (62%, volume/volume (v/v)). The ethanol is of pharmaceutical - grade quality, ensuring its effectiveness in eliminating germs.
Our company adheres strictly to a no - addition policy for other active . The carefully selected ingredient list is the result of extensive research and testing, and any deviation by adding different or extra ingredients could potentially undermine the quality and germ - killing efficacy of the hand sanitizer. Rest assured, this hand sanitizer is a reliable choice for your daily hand - cleaning needs.

Active Ingredients

Alcohol 62% v/v. Antibacterial

Purpose

Hand Sanitizer

Use

Hand Sanitizer to help reduce bacteria that potentially can cause disease. For use when soap and water are not available.

Warnings

Flammable. Keep away from fire or flame. For external use only.

Do not use it near eye area. In case of contact, rinse eyes thoroughly with water.

WHEN USING

For external use only. Do not use it near eye area. In case of contact, rinse eyes thoroughly with water.

Stop use and ask a doctor if irritation or rash appears and lasts.

Keep out of reach of children.

Directions

Apply into hand and thoroughly spreadon both hands, rub until dry.
Supervise children under 6 years of age when using this product to avoid swallowing.

Other information

- Store between 15 - 30℃ (59 - 86℉)
- Avoid freezing and excessive heat above 40℃ (104℉)

Inactive ingredients

Aqua/Water, Glycerin, Fragrance, FD & C Blue No.1 (CI 42090), FD & C Yellow No.5 (CI 19140)

PACKAGE LABEL

73905-042-01